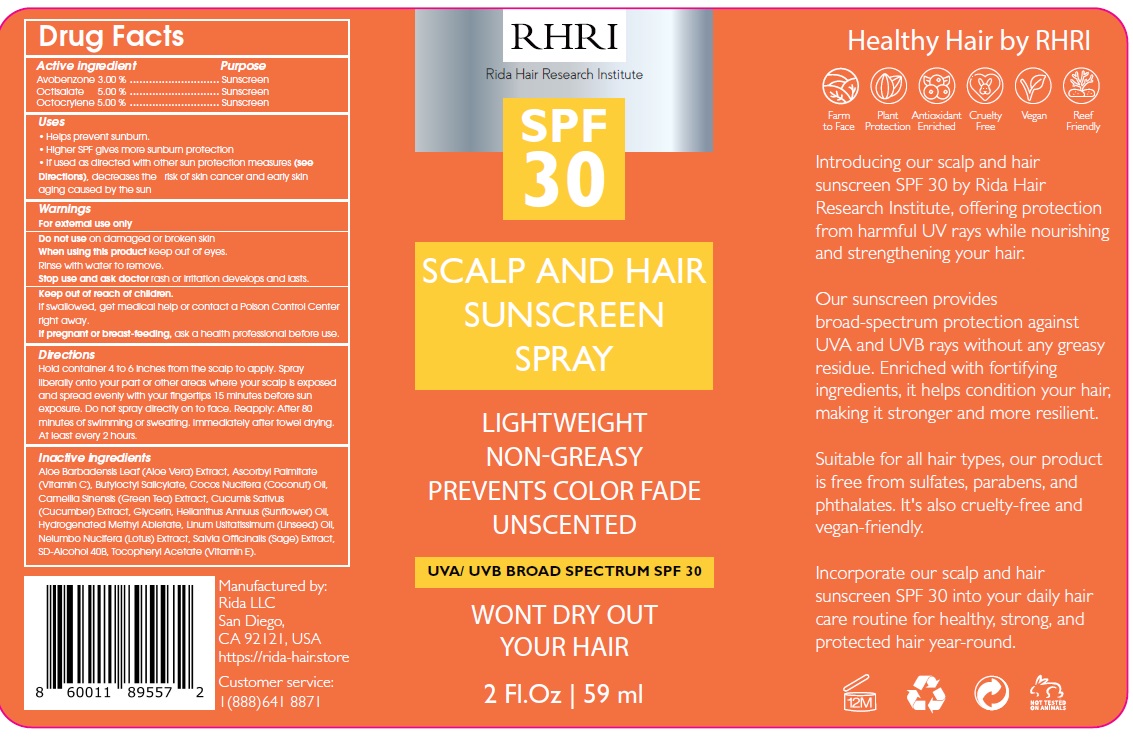 DRUG LABEL: Rida Hair Research Institute
NDC: 83004-010 | Form: LIQUID
Manufacturer: Rida LLC
Category: otc | Type: HUMAN OTC DRUG LABEL
Date: 20250225

ACTIVE INGREDIENTS: AVOBENZONE 30 mg/1 mL; OCTISALATE 50 mg/1 mL; OCTOCRYLENE 50 mg/1 mL
INACTIVE INGREDIENTS: ALOE VERA LEAF; ASCORBYL PALMITATE; BUTYLOCTYL SALICYLATE; COCONUT OIL; GREEN TEA LEAF; CUCUMBER; GLYCERIN; SUNFLOWER OIL; HYDROGENATED METHYL ABIETATE; LINSEED OIL; NELUMBO NUCIFERA FLOWER; SAGE; METHYL ALCOHOL; .ALPHA.-TOCOPHEROL ACETATE

Active ingredient Purpose

Avobenzone 3.00 % Sunscreen
Octisalate 5.00 % Sunscreen
Octocrylene 5.00 % Sunscreen

Uses

- Helps prevent sunburn.
- Higher SPF gives more sunburn protection
- If used as directed with other sun protection measures (see Directions), decreases the risk of skin cancer and early skin aging caused by the sun

Warnings

For external use only.

Do not use ondamaged or broken skin

When using this productkeep out of eyes.

Rinse with water to remove.

Stop use and ask doctorrash or irritation develops and lasts.

Keep out of reach of children. If swallowed, get medical help or contact a Poison Control Center right away.

If pregnant or breast-feeding, ask a health professional before use.

DIRECTIONS

Hold container 4 to 6 inches from the scalp to apply. Spray liberally onto your part or other areas where your scalp is exposed and spread evenly

with your fingertips 15 minutes before sun exposure. Do not spray directly on to face. Reapply: After 80 minutes of swimming or sweating.

Immediately after towel drying. At least every 2 hours.

Inactive Ingredients

Aloe Barbadensis Leaf (Aloe Vera) Extract, Ascorbyl Palmitate (Vitamin C), Butyloctyl Salicylate, Cocos Nucifera (Coconut) Oil,
Camellia Sinensis (Green Tea) Extract, Cucumis Sativus (Cucumber) Extract, Glycerin, Helianthus Annuus (Sunflower) Oil, Hydrogenated Methyl Abietate, Linum Usitatissimum (Linseed) Oil, Nelumbo Nucifera (Lotus) Extract, Salvia Officinalis (Sage) Extract, SD-Alcohol 40B, Tocopheryl Acetate (Vitamin E).